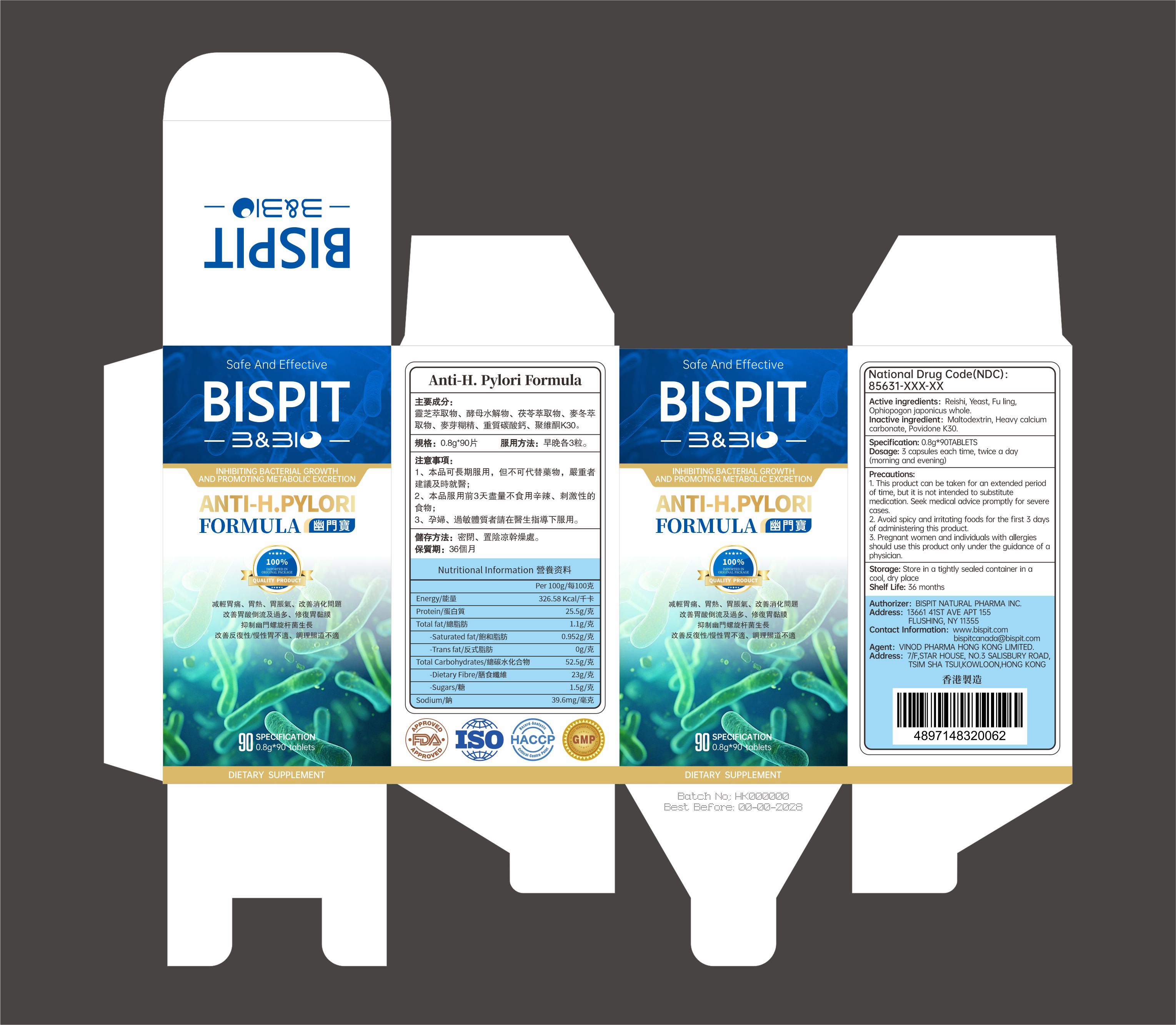 DRUG LABEL: ANTI-H.PYLORI FORMULA
NDC: 85631-016 | Form: CAPSULE
Manufacturer: Bispit Canada Ltd.
Category: otc | Type: HUMAN OTC DRUG LABEL
Date: 20251222

ACTIVE INGREDIENTS: OPHIOPOGON JAPONICUS WHOLE 3.5 g/100 g; YEAST 6 g/100 g; FU LING 3 g/100 g; REISHI 50 g/100 g
INACTIVE INGREDIENTS: CALCIUM CARBONATE; MALTODEXTRIN; POVIDONE K30

85631-016-01ANTI-H.PYLORI FORMULA

Active ingredients: Reishi, Yeast, Fu lingOphiopogon japonicus whole.

Inactive ingredient: Maltodextrin, Heavy calciumcarbonate, Povidone K30.

KEEP OUT OF REACH OF CHILDREN

Storage: Store in a tightly sealed container in acool, dry place,Keep out of children

PURPOSE

INHIBITING BACTERIAL GROWTH
AND PROMOTING METABOLIC EXCRETION

WARNINGS

1. This product can be taken for an extended periodof time, but it is not intended to substitutemedication. Seek medical advice promptly for severecases.
2. Avoid spicy and irritating foods for the first 3 daysof administering this product.3. Pregnant women and individuals with allergiesshould use this product only under the guidance of aphysician.

DOSAGE AND ADMINISTRATION

Dosage: 3 capsules each time, twice a day(morning and evening)

INDICATIONS AND USAGE

Avoid spicy and irritating foods for the first 3 daysf administering this product.